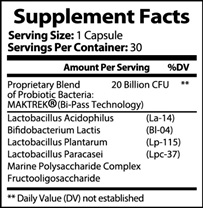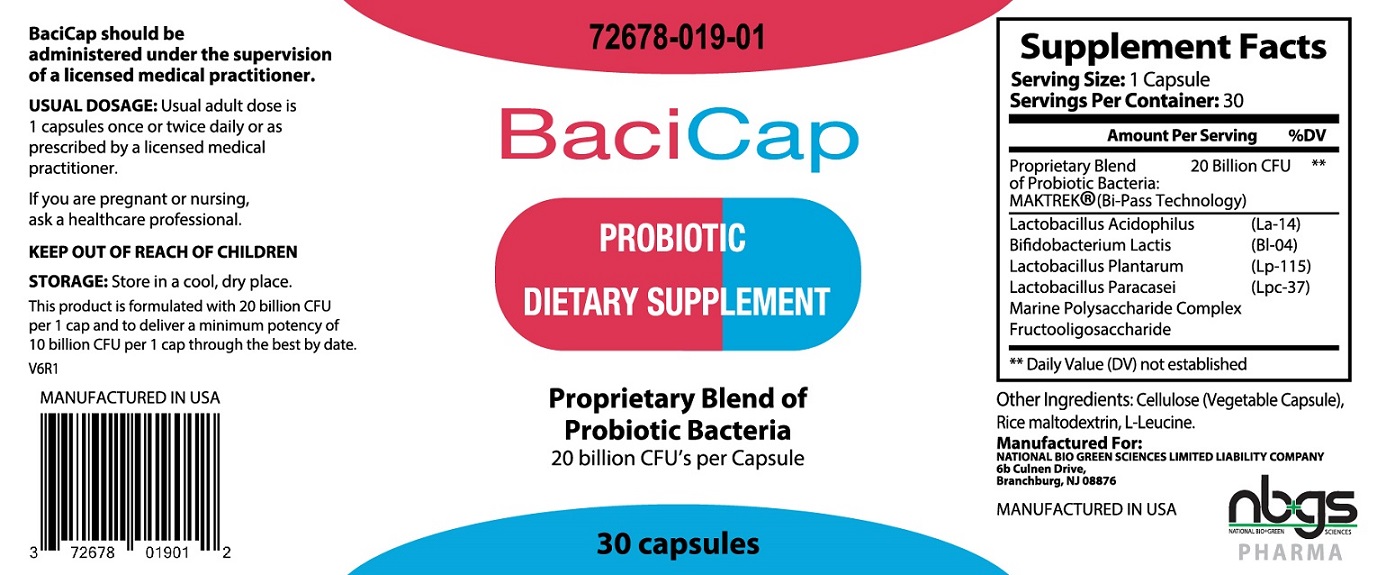 DRUG LABEL: BACICAP PROBIOTIC
NDC: 72678-019 | Form: CAPSULE
Manufacturer: NATIONAL BIO GREEN SCIENCES LIMITED LIABILTY COMPANY
Category: other | Type: DIETARY SUPPLEMENT
Date: 20200620

ACTIVE INGREDIENTS: LACTOBACILLUS ACIDOPHILUS 20000000000 [CFU]/1 1; BIFIDOBACTERIUM ANIMALIS LACTIS 20000000000 [CFU]/1 1; LACTOBACILLUS PLANTARUM 20000000000 [CFU]/1 1; LACTOBACILLUS PARACASEI 20000000000 [CFU]/1 1
INACTIVE INGREDIENTS: .ALPHA.-CELLULOSE; MALTODEXTRIN; ACETYLLEUCINE, L-

BACICAP PROBIOTIC DIETARY SUPPLEMENT

STATEMENT OF IDENTITY

BACICAP Probiotic Dietary Supplement

Dispensed by Prescription

 | Amount Per Serving | %DV
Proprietary blend of Probiotic Bacteria;; MAKTREK (Bi-Pass Technology) | 20 Billion | *
*Daily Values (DV) not established

OTHER INGREDIENTS: Cellulose (Vegetable Capsule), Rice Maltodextrin, L-Leucine

BACICAP is an orally administered prescription probiotic formulation for the clinical dietary management of suboptimal nutritional status in patients where advanced supplementation is required and nutritional supplementation in physiologically stressful conditions for maintenance of good health is needed.

BACICAP should be administered under the supervision of a licensed medical practitioner.

BACICAP is manufactured in accordance with Current Good Manufacturing Practice for foods, using ingredients that have been approved by the U.S. Food and Drug Administration (FDA) as food additives or are Generally Recognized as Safe (GRAS) for their intended use.

DOSAGE

Usual adult dose is 1 capsule once or twice daily, or as prescribed by a licensed medical practitioner.

If you are pregnant or nursing, ask a healthcare professional.

BACICAP should be administered under the supervision of a licensed medical practitioner.

DIRECTIONS FOR USE: Take as directed by a healthcare professional.

SAFE HANDLING

This product is contraindicated in patients with a known hypersensitivity to any of the ingredients.

BACICAP capsules should only be used under the direction and supervision of a licensed medical practitioner. Use with caution in patients that may have a medical condition, are pregnant, lactating, trying to conceive, under the age of 18, or taking medications.

KEEP OUT OF REACH OF CHILDREN

STORAGE

Store at 20°-25°C (68°-77°F); excursions permitted to 15°-30°C (59°-86°F) [See USP Controlled Room Temperature.]

HOW SUPPLIED HEALTH CLAIM

BACICAP, Probiotic Dietary Supplement

Capsules are off-white in color, each bottle contains 30 Capsules 72678-019-01*

Manufactured in USA for:
NATIONAL BIO GREEN SCIENCES LIMITED LIABILTY COMPANY
Branchburg, NJ 08876
Rev. 3/2020

* NATIONAL BIO GREEN SCIENCES LIMITED LIABILTY COMPANY does not represent these product codes to be National Drug Codes (NDC). Product codes are formatted according to standard industry practice, to meet the formatting requirement by pedigree reporting and supply-chain control including pharmacies.

† The most appropriate way to ensure pedigree reporting consistent with these regulatory guidelines and safety monitoring is to dispense this product by prescription. This is not an Orange Book product. This product may be administered only under a physician’s supervision and all prescriptions using this product shall be pursuant to state statutes as applicable. The ingredients, indication or claims of this product are not to be construed to be drug claims.